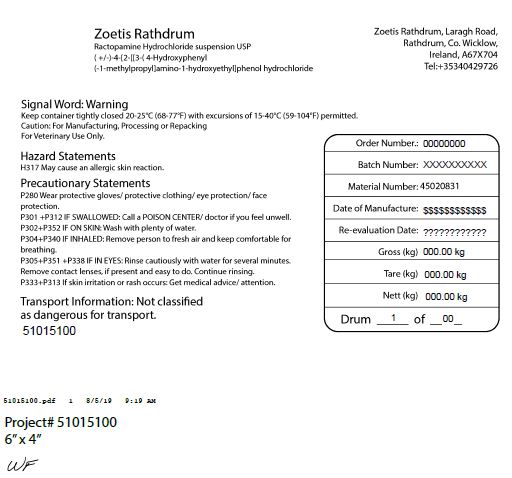 DRUG LABEL: Ractopamine Hydrochloride
NDC: 54771-0831 | Form: SUSPENSION
Manufacturer: Zoetis Inc.
Category: other | Type: BULK INGREDIENT - ANIMAL DRUG
Date: 20240214

ACTIVE INGREDIENTS: RACTOPAMINE HYDROCHLORIDE 1 kg/1 kg

Ractopamine Hydrochloride